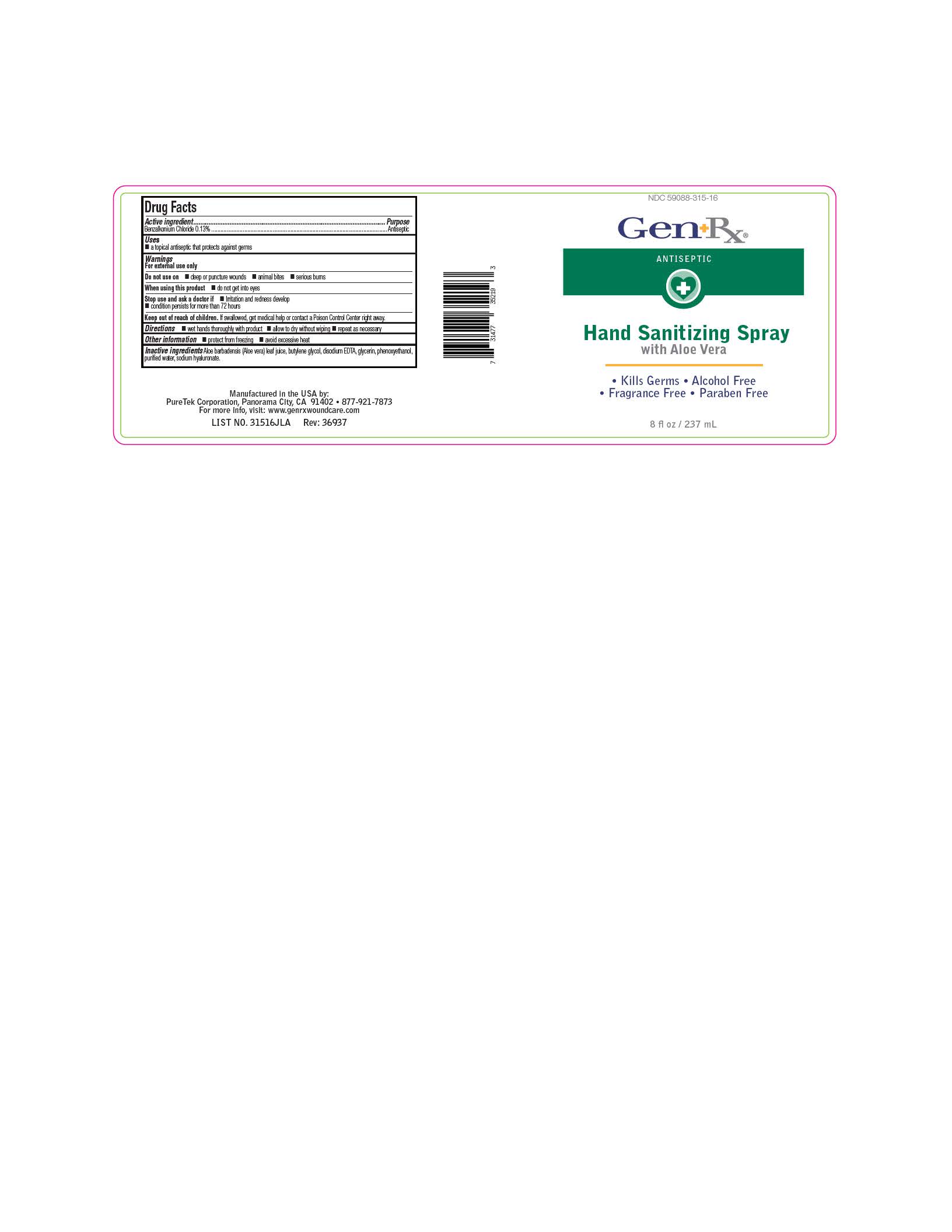 DRUG LABEL: GenRx Hand Sanitizing
NDC: 59088-315 | Form: SPRAY
Manufacturer: PureTek Corporation
Category: otc | Type: HUMAN OTC DRUG LABEL
Date: 20241002

ACTIVE INGREDIENTS: BENZALKONIUM CHLORIDE 1.3 mg/1 mL
INACTIVE INGREDIENTS: WATER; HYALURONATE SODIUM; SODIUM HYDROXIDE; ALOE VERA LEAF; GLYCERIN; PHENOXYETHANOL; BUTYLENE GLYCOL; EDETATE DISODIUM

GenRx Hand Sanitizing

Active ingredient

Benzalkonium Chloride 0.13%

Purpose

Antiseptic

Uses

■ a topical antiseptic that protects against germs

Warnings

For external use only

Do not use on

■ deep or puncture wounds ■ animal bites ■ serious burns

When using this product

■ do not get into eyes

Stop use and ask a doctor if

■ Irritation and redness develop
■ condition persists for more than 72 hours

Keep out of reach of children.

If swallowed, get medical help or contact a Poison Control Center right away.

Directions

■ wet hands thoroughly with product
■ allow to dry without wiping
■ repeat as necessary

Other information

■ protect from freezing ■ avoid excessive heat

Inactive ingredients

Aloe barbadensis (Aloe vera) leaf juice, butylene glycol, disodium EDTA, glycerin, phenoxyethanol,

purified water, sodium hyaluronate.